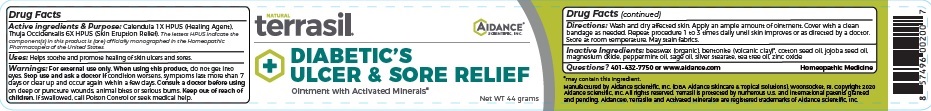 DRUG LABEL: Terrasil Diabetics Ulcer and Sore Relief
NDC: 24909-195 | Form: OINTMENT
Manufacturer: Aidance Skincare & Topical Solutions, LLC
Category: homeopathic | Type: HUMAN OTC DRUG LABEL
Date: 20240524

ACTIVE INGREDIENTS: CALENDULA OFFICINALIS FLOWER 1 [hp_X]/44 g; THUJA OCCIDENTALIS WHOLE 6 [hp_X]/44 g
INACTIVE INGREDIENTS: WHITE WAX; BENTONITE; COTTONSEED OIL; JOJOBA OIL; MAGNESIUM OXIDE; PEPPERMINT OIL; SAGE OIL; SILVER OXIDE; TEA TREE OIL; ZINC OXIDE; STEARIC ACID

24909-195 terrasil Diabetics Ulcer and Sore Relief

Active Ingredients

Calendula 1X HPUS .......................Healing Agent

Thuja Occidentalis 6X HPUS .............Skin Eruption Relief

The letters HPUS indicate the component(s) in this product is (are) ofﬁcially monographed in the Homeopathic Pharmacopeia of the United States.

Uses

Helps soothe and promote healing of skin ulcers and sores.

Warnings

For external use only.

When using this product, do not get into eyes.

Stop use and ask a doctor ifcondition worsens, symptoms last more than 7 days or clear up and occur again within a few days.

Consult a doctor before usingon deep or puncture wounds, animal bites or serious burns.

Keep out of reach of children.If swallowed, call Poison Control or seek medical help.

Directions

Wash and dry affected skin. Apply an ample amount of ointment. Cover with a clean bandage as needed. Repeat procedure 1 to 3 times daily until skin improves or as directed by a doctor. Store at room temperature. May stain fabrics.

Inactive ingredients

beeswax (organic), bentonite (volcanic clay), cotton seed oil, jojoba seed oil, magnesium oxide, peppermint oil, sage oil, Silver Stearate, tea tree oil, zinc oxide

Questions?: 401-432-7750 or www.aidance.com